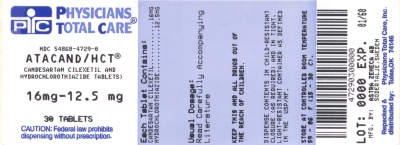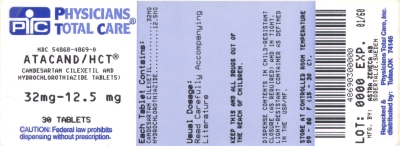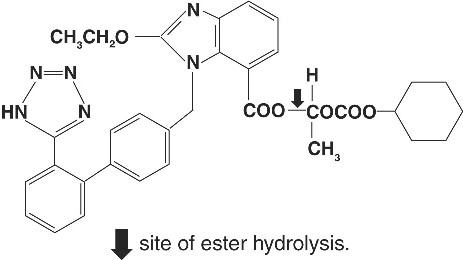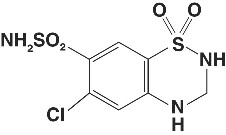 DRUG LABEL: ATACAND HCT
NDC: 54868-4729 | Form: TABLET
Manufacturer: Physicians Total Care, Inc.
Category: prescription | Type: HUMAN PRESCRIPTION DRUG LABEL
Date: 20120202

ACTIVE INGREDIENTS: CANDESARTAN CILEXETIL 16 mg/1 1; HYDROCHLOROTHIAZIDE 12.5 mg/1 1
INACTIVE INGREDIENTS: CARBOXYMETHYLCELLULOSE CALCIUM; HYDROXYPROPYL CELLULOSE; LACTOSE MONOHYDRATE; MAGNESIUM STEARATE; STARCH, CORN; POLYETHYLENE GLYCOL 8000; FERRIC OXIDE YELLOW; FERRIC OXIDE RED

ATACAND HCT® 16-12.5
(candesartan cilexetil−hydrochlorothiazide)
TABLETS
ATACAND HCT® 32-12.5
(candesartan cilexetil−hydrochlorothiazide)
TABLETS
ATACAND HCT® 32–25
candesartan cilexetil-hydrochlorothiazide

USE IN PREGNANCY

When used in pregnancy during the second and third trimesters, drugs that act directly on the renin-angiotensin system can cause injury and even death to the developing fetus. When pregnancy is detected, ATACAND HCT should be discontinued as soon as possible. See WARNINGS, Fetal/Neonatal Morbidity and Mortality.

DESCRIPTION

ATACAND HCT (candesartan cilexetil-hydrochlorothiazide) combines an angiotensin II receptor (type AT1) antagonist and a diuretic, hydrochlorothiazide.

Candesartan cilexetil, a nonpeptide, is chemically described as (±)-1-Hydroxyethyl 2-ethoxy-1-[p-(o-1H-tetrazol-5-ylphenyl)benzyl]-7-benzimidazolecarboxylate, cyclohexyl carbonate (ester).

Its empirical formula is C33H34N6O6, and its structural formula is

Candesartan cilexetil is a white to off-white powder with a molecular weight of 610.67. It is practically insoluble in water and sparingly soluble in methanol. Candesartan cilexetil is a racemic mixture containing one chiral center at the cyclohexyloxycarbonyloxy ethyl ester group. Following oral administration, candesartan cilexetil undergoes hydrolysis at the ester link to form the active drug, candesartan, which is achiral.

Hydrochlorothiazide is 6-chloro-3,4-dihydro-2H-1,2,4-benzothiadiazine-7-sulfonamide 1,1-dioxide. Its empirical formula is C7H8ClN3O4S2 and its structural formula is

Hydrochlorothiazide is a white, or practically white, crystalline powder with a molecular weight of 297.72, which is slightly soluble in water, but freely soluble in sodium hydroxide solution.

ATACAND HCT is available for oral administration in three tablet strengths of candesartan cilexetil and hydrochlorothiazide.

ATACAND HCT 16-12.5 contains 16 mg of candesartan cilexetil and 12.5 mg of hydrochlorothiazide. ATACAND HCT 32-12.5 contains 32 mg of candesartan cilexetil and 12.5 mg of hydrochlorothiazide. ATACAND HCT 32–25 contains 32 mg of candesartan cilexetil and 25 mg of hydrochlorothiazide. The inactive ingredients of the tablets are carboxymethylcellulose calcium, hydroxypropyl cellulose, lactose monohydrate, magnesium stearate, corn starch, polyethylene glycol 8000, and ferric oxide (yellow). Ferric oxide (reddish brown) is also added to the 16-12.5 mg and 32–25 mg tablets as colorant.

CLINICAL PHARMACOLOGY

Mechanism of Action

Angiotensin II is formed from angiotensin I in a reaction catalyzed by angiotensin-converting enzyme (ACE, kininase II). Angiotensin II is the principal pressor agent of the renin-angiotensin system, with effects that include vasoconstriction, stimulation of synthesis and release of aldosterone, cardiac stimulation, and renal reabsorption of sodium. Candesartan blocks the vasoconstrictor and aldosterone-secreting effects of angiotensin II by selectively blocking the binding of angiotensin II to the AT1 receptor in many tissues, such as vascular smooth muscle and the adrenal gland. Its action is, therefore, independent of the pathways for angiotensin II synthesis.

There is also an AT2 receptor found in many tissues, but AT2 is not known to be associated with cardiovascular homeostasis. Candesartan has much greater affinity (>10,000-fold) for the AT1 receptor than for the AT2 receptor.

Blockade of the renin-angiotensin system with ACE inhibitors, which inhibit the biosynthesis of angiotensin II from angiotensin I, is widely used in the treatment of hypertension. ACE inhibitors also inhibit the degradation of bradykinin, a reaction also catalyzed by ACE. Because candesartan does not inhibit ACE (kininase II), it does not affect the response to bradykinin. Whether this difference has clinical relevance is not yet known. Candesartan does not bind to or block other hormone receptors or ion channels known to be important in cardiovascular regulation.

Blockade of the angiotensin II receptor inhibits the negative regulatory feedback of angiotensin II on renin secretion, but the resulting increased plasma renin activity and angiotensin II circulating levels do not overcome the effect of candesartan on blood pressure.

Hydrochlorothiazide is a thiazide diuretic. Thiazides affect the renal tubular mechanisms of electrolyte reabsorption, directly increasing excretion of sodium and chloride in approximately equivalent amounts. Indirectly, the diuretic action of hydrochlorothiazide reduces plasma volume, with consequent increases in plasma renin activity, increases in aldosterone secretion, increases in urinary potassium loss, and decreases in serum potassium. The renin-aldosterone link is mediated by angiotensin II, so coadministration of an angiotensin II receptor antagonist tends to reverse the potassium loss associated with these diuretics.

The mechanism of the antihypertensive effect of thiazides is unknown.

Pharmacokinetics

General

Candesartan Cilexetil

Candesartan cilexetil is rapidly and completely bioactivated by ester hydrolysis during absorption from the gastrointestinal tract to candesartan, a selective AT1 subtype angiotensin II receptor antagonist. Candesartan is mainly excreted unchanged in urine and feces (via bile). It undergoes minor hepatic metabolism by O-deethylation to an inactive metabolite. The elimination half-life of candesartan is approximately 9 hours. After single and repeated administration, the pharmacokinetics of candesartan are linear for oral doses up to 32 mg of candesartan cilexetil. Candesartan and its inactive metabolite do not accumulate in serum upon repeated once-daily dosing.

Following administration of candesartan cilexetil, the absolute bioavailability of candesartan was estimated to be 15%. After tablet ingestion, the peak serum concentration (Cmax) is reached after 3 to 4 hours. Food with a high fat content does not affect the bioavailability of candesartan after candesartan cilexetil administration.

Hydrochlorothiazide

When plasma levels have been followed for at least 24 hours, the plasma half-life has been observed to vary between 5.6 and 14.8 hours.

Metabolism and Excretion

Candesartan Cilexetil

Total plasma clearance of candesartan is 0.37 mL/min/kg, with a renal clearance of 0.19 mL/min/kg. When candesartan is administered orally, about 26% of the dose is excreted unchanged in urine. Following an oral dose of ^14C-labeled candesartan cilexetil, approximately 33% of radioactivity is recovered in urine and approximately 67% in feces. Following an intravenous dose of ^14C-labeled candesartan, approximately 59% of radioactivity is recovered in urine and approximately 36% in feces. Biliary excretion contributes to the elimination of candesartan.

Hydrochlorothiazide

Hydrochlorothiazide is not metabolized but is eliminated rapidly by the kidney. At least 61% of the oral dose is eliminated unchanged within 24 hours.

Distribution

Candesartan Cilexetil

The volume of distribution of candesartan is 0.13 L/kg. Candesartan is highly bound to plasma proteins (>99%) and does not penetrate red blood cells. The protein binding is constant at candesartan plasma concentrations well above the range achieved with recommended doses. In rats, it has been demonstrated that candesartan crosses the blood-brain barrier poorly, if at all. It has also been demonstrated in rats that candesartan passes across the placental barrier and is distributed in the fetus.

Hydrochlorothiazide

Hydrochlorothiazide crosses the placental but not the blood-brain barrier and is excreted in breast milk.

Special Populations

Pediatric

The pharmacokinetics of candesartan cilexetil have not been investigated in patients <18 years of age.

Geriatric

The pharmacokinetics of candesartan have been studied in the elderly (≥ 65 years). The plasma concentration of candesartan was higher in the elderly (Cmax was approximately 50% higher, and AUC was approximately 80% higher) compared to younger subjects administered the same dose. The pharmacokinetics of candesartan were linear in the elderly, and candesartan and its inactive metabolite did not accumulate in the serum of these subjects upon repeated, once-daily administration. No initial dosage adjustment is necessary. (See DOSAGE AND ADMINISTRATION.)

Gender

There is no difference in the pharmacokinetics of candesartan between male and female subjects.

Renal Insufficiency

In hypertensive patients with renal insufficiency, serum concentrations of candesartan were elevated. After repeated dosing, the AUC and Cmaxwere approximately doubled in patients with severe renal impairment (creatinine clearance <30 mL/min/1.73m^2) compared to patients with normal kidney function. The pharmacokinetics of candesartan in hypertensive patients undergoing hemodialysis are similar to those in hypertensive patients with severe renal impairment. Candesartan cannot be removed by hemodialysis. No initial dosage adjustment is necessary in patients with renal insufficiency.

Thiazide diuretics are eliminated by the kidney, with a terminal half-life of 5-15 hours. In a study of patients with impaired renal function (mean creatinine clearance of 19 mL/min), the half-life of hydrochlorothiazide elimination was lengthened to 21 hours. (See DOSAGE AND ADMINISTRATION.)

Hepatic Insufficiency

The pharmacokinetics of candesartan were compared in patients with mild (Child-Pugh A) or moderate (Child-Pugh B) hepatic impairment to matched healthy volunteers following a single dose of 16 mg candesartan cilexetil. The AUC for candesartan in patients with mild and moderate hepatic impairment was increased 30% and 145% respectively. The Cmax for candesartan was increased 56% and 73% respectively. The pharmacokinetics of candesartan in severe hepatic impairment have not been studied. No dose adjustment is recommended for patients with mild hepatic impairment. In patients with moderate hepatic impairment, consideration should be given to initiation of ATACAND at a lower dose, such as 8 mg. If a lower starting dose is selected for candesartan cilexetil, ATACAND HCT is not recommended for initial titration because the appropriate initial starting dose of candesartan cilexetil cannot be given. (See DOSAGE AND ADMINISTRATION).

Thiazide diuretics should be used with caution in patients with hepatic impairment. (See DOSAGE AND ADMINISTRATION.)

Pharmacodynamics

Candesartan Cilexetil

Candesartan inhibits the pressor effects of angiotensin II infusion in a dose-dependent manner. After 1 week of once-daily dosing with 8 mg of candesartan cilexetil, the pressor effect was inhibited by approximately 90% at peak with approximately 50% inhibition persisting for 24 hours.

Plasma concentrations of angiotensin I and angiotensin II, and plasma renin activity (PRA), increased in a dose-dependent manner after single and repeated administration of candesartan cilexetil to healthy subjects and hypertensive patients. ACE activity was not altered in healthy subjects after repeated candesartan cilexetil administration. The once-daily administration of up to 16 mg of candesartan cilexetil to healthy subjects did not influence plasma aldosterone concentrations, but a decrease in the plasma concentration of aldosterone was observed when 32 mg of candesartan cilexetil was administered to hypertensive patients. In spite of the effect of candesartan cilexetil on aldosterone secretion, very little effect on serum potassium was observed.

In multiple-dose studies with hypertensive patients, there were no clinically significant changes in metabolic function including serum levels of total cholesterol, triglycerides, glucose, or uric acid. In a 12-week study of 161 patients with non-insulin-dependent (type 2) diabetes mellitus and hypertension, there was no change in the level of HbA1c.

Hydrochlorothiazide

After oral administration of hydrochlorothiazide, diuresis begins within 2 hours, peaks in about 4 hours and lasts about 6 to 12 hours.

Clinical Trials

Candesartan Cilexetil−Hydrochlorothiazide

Of 12 controlled clinical trials involving 4588 patients, 5 were double-blind, placebo controlled and evaluated the antihypertensive effects of single entities vs the combination. These 5 trials, of 8 to 12 weeks duration, randomized 3037 hypertensive patients. Doses ranged from 2 to 32 mg candesartan cilexetil and from 6.25 to 25 mg hydrochlorothiazide administered once daily in various combinations.

The combination of candesartan cilexetil-hydrochlorothiazide resulted in placebo-adjusted decreases in sitting systolic and diastolic blood pressures of 14-18/8-11 mm Hg at doses of 16-12.5 mg and 32-12.5 mg. The combination of candesartan cilexetil and hydrochlorothiazide 32-25 mg resulted in placebo-adjusted decreases in sitting systolic and diastolic blood pressures of 16-19/9-11 mm Hg. The placebo corrected trough to peak ratio was evaluated in a study of candesartan cilexetil-hydrochlorothiazide 32-12.5 mg and was 88%.

Most of the antihypertensive effect of the combination of candesartan cilexetil and hydrochlorothiazide was seen in 1 to 2 weeks with the full effect observed within 4 weeks. In long-term studies of up to 1 year, the blood pressure lowering effect of the combination was maintained. The antihypertensive effect was similar regardless of age or gender, and overall response to the combination was similar in black and non-black patients. No appreciable changes in heart rate were observed with combination therapy in controlled trials.

INDICATIONS AND USAGE

ATACAND HCT is indicated for the treatment of hypertension. This fixed dose combination is not indicated for initial therapy (see DOSAGE AND ADMINISTRATION).

CONTRAINDICATIONS

ATACAND HCT is contraindicated in patients who are hypersensitive to any component of this product.

Because of the hydrochlorothiazide component, this product is contraindicated in patients with anuria or hypersensitivity to other sulfonamide-derived drugs.

WARNINGS

Fetal/Neonatal Morbidity and Mortality

Drugs that act directly on the renin-angiotensin system can cause fetal and neonatal morbidity and death when administered to pregnant women. Several dozen cases have been reported in the world literature in patients who were taking angiotensin- converting enzyme inhibitors. Post-marketing experience has identified reports of fetal and neonatal toxicity in babies born to women treated with candesartan cilexetil during pregnancy. Because candesartan cilexetil is a component of ATACAND HCT, when pregnancy is detected, ATACAND HCT should be discontinued as soon as possible.

The use of drugs that act directly on the renin-angiotensin system during the second and third trimesters of pregnancy has been associated with fetal and neonatal injury, including hypotension, neonatal skull hypoplasia, anuria, reversible or irreversible renal failure, and death. Oligohydramnios has also been reported, presumably resulting from decreased fetal renal function; oligohydramnios in this setting has been associated with fetal limb contractures, craniofacial deformation, and hypoplastic lung development. Prematurity, intrauterine growth retardation, and patent ductus arteriosus have also been reported, although it is not clear whether these occurrences were due to exposure to the drug.

These adverse effects do not appear to have resulted from intrauterine drug exposure that has been limited to the first trimester. Mothers whose embryos and fetuses are exposed to an angiotensin II receptor antagonist only during the first trimester should be so informed. Nonetheless, when patients become pregnant, physicians should have the patient discontinue the use of ATACAND HCT as soon as possible.

Rarely (probably less often than once in every thousand pregnancies), no alternative to a drug acting on the renin-angiotensin system will be found. In these rare cases, the mothers should be apprised of the potential hazards to their fetuses, and serial ultrasound examinations should be performed to assess the intra-amniotic environment.

If oligohydramnios is observed, ATACAND HCT should be discontinued unless it is considered life saving for the mother. Contraction stress testing (CST), a nonstress test (NST), or biophysical profiling (BPP) may be appropriate, depending upon the week of pregnancy. Patients and physicians should be aware, however, that oligohydramnios may not appear until after the fetus has sustained irreversible injury.

Infants with histories of in utero exposure to an angiotensin II receptor antagonist should be closely observed for hypotension, oliguria, and hyperkalemia. If oliguria occurs, attention should be directed toward support of blood pressure and renal perfusion. Exchange transfusion or dialysis may be required as means of reversing hypotension and/or substituting for disordered renal function.

Candesartan Cilexetil-Hydrochlorothiazide

There was no evidence of teratogenicity or other adverse effects on embryo-fetal development when pregnant mice, rats or rabbits were treated orally with candesartan cilexetil alone or in combination with hydrochlorothiazide. For mice, the maximum dose of candesartan cilexetil was 1000 mg/kg/day (about 150 times the maximum recommended daily human dose [MRHD] [Doses compared on the basis of body surface area. MRHD considered to be 32 mg for candesartan cilexetil and 12.5 mg for hydrochlorothiazide.]). For rats, the maximum dose of candesartan cilexetil was 100 mg/kg/day (about 31 times the MRHD). For rabbits, the maximum dose of candesartan cilexetil was 1 mg/kg/day (a maternally toxic dose that is about half the MRHD). In each of these studies, hydrochlorothiazide was tested at the same dose level (10 mg/kg/day, about 4, 8, and 15 times the MRHD in mouse, rats, and rabbit, respectively). There was no evidence of harm to the rat or mouse fetus or embryo in studies in which hydrochlorothiazide was administered alone to the pregnant rat or mouse at doses of up to 1000 and 3000 mg/kg/day, respectively.

Thiazides cross the placental barrier and appear in cord blood. There is a risk of fetal or neonatal jaundice, thrombocytopenia, and possibly other adverse reactions that have occurred in adults.

Hypotension in Volume- and Salt-Depleted Patients

Based on adverse events reported from all clinical trials of ATACAND HCT, excessive reduction of blood pressure was rarely seen in patients with uncomplicated hypertension treated with candesartan cilexetil and hydrochlorothiazide (0.4%). Initiation of antihypertensive therapy may cause symptomatic hypotension in patients with intravascular volume- or sodium- depletion, eg, in patients treated vigorously with diuretics or in patients on dialysis. These conditions should be corrected prior to administration of ATACAND HCT, or the treatment should start under close medical supervision (see DOSAGE AND ADMINISTRATION).

If hypotension occurs, the patients should be placed in the supine position and, if necessary, given an intravenous infusion of normal saline. A transient hypotensive response is not a contraindication to further treatment which usually can be continued without difficulty once the blood pressure has stabilized.

Hydrochlorothiazide

Acute Myopia and Secondary Angle-Closure Glaucoma

Hydrochlorothiazide, a sulfonamide, can cause an idiosyncratic reaction, resulting in acute transient myopia and acute angle-closure glaucoma. Symptoms include acute onset of decreased visual acuity or ocular pain and typically occur within hours to weeks of drug initiation. Untreated acute angle-closure glaucoma can lead to permanent vision loss. The primary treatment is to discontinue hydrochlorothiazide as rapidly as possible. Prompt medical or surgical treatments may need to be considered if the intraocular pressure remains uncontrolled. Risk factors for developing acute angle-closure glaucoma may include a history of sulfonamide or penicillin allergy.

Impaired Hepatic Function

Thiazide diuretics should be used with caution in patients with impaired hepatic function or progressive liver disease, since minor alterations of fluid and electrolyte balance may precipitate hepatic coma.

Hypersensitivity Reaction

Hypersensitivity reactions to hydrochlorothiazide may occur in patients with or without a history of allergy or bronchial asthma, but are more likely in patients with such a history.

Systemic Lupus Erythematosus

Thiazide diuretics have been reported to cause exacerbation or activation of systemic lupus erythematosus.

Lithium Interaction

Lithium generally should not be given with thiazides (see PRECAUTIONS, Drug Interactions, Hydrochlorothiazide, Lithium).

PRECAUTIONS

General

Candesartan Cilexetil−Hydrochlorothiazide

In clinical trials of various doses of candesartan cilexetil and hydrochlorothiazide, the incidence of hypertensive patients who developed hypokalemia (serum potassium <3.5 mEq/L) was 2.5% versus 2.1% for placebo; the incidence of hyperkalemia (serum potassium >5.7 mEq/L) was 0.4% versus 1.0% for placebo. No patient receiving ATACAND HCT 16-12.5 mg or 32-12.5 mg was discontinued due to increases or decreases in serum potassium. Overall, the combination of candesartan cilexetil and hydrochlorothiazide had no clinically significant effect on serum potassium.

Candesartan

Major Surgery/Anesthesia— Hypotension may occur during major surgery and anesthesia in patients treated with angiotensin II receptor antagonists, including candesartan, due to blockade of the renin-angiotensin system. Very rarely, hypotension may be severe such that it may warrant the use of intravenous fluids and/or vasopressors.

Hydrochlorothiazide

Periodic determination of serum electrolytes to detect possible electrolyte imbalance should be performed at appropriate intervals.

All patients receiving thiazide therapy should be observed for clinical signs of fluid or electrolyte imbalance: namely, hyponatremia, hypochloremic alkalosis, and hypokalemia. Serum and urine electrolyte determinations are particularly important when the patient is vomiting excessively or receiving parenteral fluids. Warning signs or symptoms of fluid and electrolyte imbalance, irrespective of cause, include dryness of mouth, thirst, weakness, lethargy, drowsiness, restlessness, confusion, seizures, muscle pains or cramps, muscular fatigue, hypotension, oliguria, tachycardia, and gastrointestinal disturbances such as nausea and vomiting.

Hypokalemia may develop, especially with brisk diuresis, when severe cirrhosis is present, or after prolonged therapy. Interference with adequate oral electrolyte intake will also contribute to hypokalemia. Hypokalemia may cause cardiac arrhythmia and may also sensitize or exaggerate the response of the heart to the toxic effects of digitalis (eg, increased ventricular irritability).

Although any chloride deficit is generally mild and usually does not require specific treatment, except under extraordinary circumstances (as in liver disease or renal disease), chloride replacement may be required in the treatment of metabolic alkalosis.

Dilutional hyponatremia may occur in edematous patients in hot weather; appropriate therapy is water restriction, rather than administration of salt, except in rare instances when the hyponatremia is life-threatening. In actual salt depletion, appropriate replacement is the therapy of choice.

Hyperuricemia may occur or acute gout may be precipitated in certain patients receiving thiazide therapy.

In diabetic patients dosage adjustments of insulin or oral hypoglycemic agents may be required. Hyperglycemia may occur with thiazide diuretics. Thus latent diabetes mellitus may become manifest during thiazide therapy.

The antihypertensive effects of the drug may be enhanced in the post-sympathectomy patient.

If progressive renal impairment becomes evident consider withholding or discontinuing diuretic therapy.

Thiazides have been shown to increase the urinary excretion of magnesium; this may result in hypomagnesemia.

Thiazides may decrease urinary calcium excretion. Thiazides may cause intermittent and slight elevation of serum calcium in the absence of known disorders of calcium metabolism. Marked hypercalcemia may be evidence of hidden hyperparathyroidism. Thiazides should be discontinued before carrying out tests for parathyroid function.

Increases in cholesterol and triglyceride levels may be associated with thiazide diuretic therapy.

Impaired Renal Function

Candesartan Cilexetil

As a consequence of inhibiting the renin-angiotensin-aldosterone system, changes in renal function may be anticipated in susceptible individuals treated with candesartan cilexetil. In patients whose renal function may depend upon the activity of the renin-angiotensin-aldosterone system (eg, patients with severe congestive heart failure), treatment with angiotensin-converting enzyme inhibitors and angiotensin receptor antagonists has been associated with oliguria and/or progressive azotemia and (rarely) with acute renal failure and/or death. Similar results may be anticipated in patients treated with candesartan cilexetil. (See CLINICAL PHARMACOLOGY, Special Populations.)

In studies of ACE inhibitors in patients with unilateral or bilateral renal artery stenosis, increases in serum creatinine or blood urea nitrogen (BUN) have been reported. There has been no long-term use of candesartan cilexetil in patients with unilateral or bilateral renal artery stenosis, but similar results may be expected.

Hydrochlorothiazide

Thiazides should be used with caution in severe renal disease. In patients with renal disease, thiazides may precipitate azotemia. Cumulative effects of the drug may develop in patients with impaired renal function.

Impaired Hepatic Function

Candesartan Cilexetil

Based on pharmacokinetic data significant increases in candesartan AUC and Cmax in patients with moderate hepatic impairment have been demonstrated. (See CLINICAL PHARMACOLOGY, Special Populations.)

Information for Patients

Pregnancy

Female patients of childbearing age should be told about the consequences of second- and third-trimester exposure to drugs that act on the renin-angiotensin system, and they should also be told that these consequences do not appear to have resulted from intrauterine drug exposure that has been limited to the first trimester. These patients should be asked to report pregnancies to their physicians as soon as possible.

Symptomatic Hypotension

A patient receiving ATACAND HCT should be cautioned that lightheadedness can occur, especially during the first days of therapy, and that it should be reported to the prescribing physician. The patients should be told that if syncope occurs, ATACAND HCT should be discontinued until the physician has been consulted.

All patients should be cautioned that inadequate fluid intake, excessive perspiration, diarrhea, or vomiting can lead to an excessive fall in blood pressure, with the same consequences of lightheadedness and possible syncope.

Potassium Supplements

A patient receiving ATACAND HCT should be told not to use potassium supplements or salt substitutes containing potassium without consulting the prescribing physician.

Drug Interactions

Candesartan Cilexetil

No significant drug interactions have been reported in studies of candesartan cilexetil given with other drugs such as glyburide, nifedipine, digoxin, warfarin, hydrochlorothiazide, and oral contraceptives in healthy volunteers. Because candesartan is not significantly metabolized by the cytochrome P450 system and at therapeutic concentrations has no effects on P450 enzymes, interactions with drugs that inhibit or are metabolized by those enzymes would not be expected.

Non-Steroidal Anti-Inflammatory Agents including Selective Cyclooxygenase-2 Inhibitors (COX-2 Inhibitors) In patients who are elderly, volume-depleted (including those on diuretic therapy), or with compromised renal function, co-administration of NSAIDs, including selective COX-2 inhibitors, with angiotensin II receptor antagonists, including candesartan, may result in deterioration of renal function, including possible acute renal failure. These effects are usually reversible. Monitor renal function periodically in patients receiving candesartan and NSAID therapy.

The antihypertensive effect of angiotensin II receptor antagonists, including candesartan may be attenuated by NSAIDs including selective COX-2 inhibitors.

Lithium − Reversible increases in serum lithium concentrations and toxicity have been reported during concomitant administration of lithium with ACE inhibitors, and with some angiotensin II receptor antagonists. An increase in serum lithium concentration has been reported during concomitant administration of lithium with candesartan cilexetil, so careful monitoring of serum lithium levels is recommended during concomitant use.

Hydrochlorothiazide

When administered concurrently the following drugs may interact with thiazide diuretics:

Alcohol, barbiturates, or narcotics − Potentiation of orthostatic hypotension may occur.

Antidiabetic drugs (oral agents and insulin) − Dosage adjustment of the antidiabetic drug may be required.

Other antihypertensive drugs − Additive effect or potentiation.

Cholestyramine and colestipol resins − Absorption of hydrochlorothiazide is impaired in the presence of anionic exchange resins. Single doses of either cholestyramine or colestipol resins bind the hydrochlorothiazide and reduce its absorption from the gastrointestinal tract by up to 85 and 43 percent, respectively.

Corticosteroids, ACTH − Intensified electrolyte depletion, particularly hypokalemia.

Pressor amines (eg, norepinephrine) − Possible decreased response to pressor amines but not sufficient to preclude their use.

Skeletal muscle relaxants, nondepolarizing (eg, tubocurarine) −Possible increased responsiveness to the muscle relaxant.

Lithium −Generally should not be given with diuretics. Diuretic agents reduce the renal clearance of lithium and add a high risk of lithium toxicity. Refer to the package insert for lithium preparations before use of such preparations with ATACAND HCT.

Non-steroidal Anti-inflammatory Drugs − In some patients, the administration of a non-steroidal anti-inflammatory agent can reduce the diuretic, natriuretic, and antihypertensive effects of loop, potassium-sparing and thiazide diuretics. Therefore, when ATACAND HCT and non-steroidal anti-inflammatory agents are used concomitantly, the patient should be observed closely to determine if the desired effect of the diuretic is obtained.

Carcinogenesis, Mutagenesis, Impairment of Fertility

No carcinogenicity studies have been conducted with the combination of candesartan cilexetil and hydrochlorothiazide. There was no evidence of carcinogenicity when candesartan cilexetil was orally administered to mice and rats for up to 104 weeks at doses up to 100 and 1000 mg/kg/day, respectively. Rats received the drug by gavage whereas mice received the drug by dietary administration. These (maximally-tolerated) doses of candesartan cilexetil provided systemic exposures to candesartan (AUCs) that were, in mice, approximately 7 times and, in rats, more than 70 times the exposure in man at the maximum recommended daily human dose (32 mg). Two-year feeding studies in mice and rats conducted under the auspices of the National Toxicology Program (NTP) uncovered no evidence of a carcinogenic potential of hydrochlorothiazide in female mice (at doses of up to approximately 600 mg/kg/day) or in male and female rats (at doses of up to approximately 100 mg/kg/day). The NTP, however, found equivocal evidence for hepatocarcinogenicity in male mice.

Candesartan cilexetil or candesartan (the active metabolite), in combination with hydrochlorothiazide, tested positive in vitro in the Chinese hamster lung (CHL) chromosomal aberration assay and mouse lymphoma mutagenicity assay. The candesartan cilexetil/hydrochlorothiazide combination tested negative for mutagenicity in bacteria (Ames test), for unscheduled DNA synthesis in rat liver, for chromosomal aberrations in rat bone marrow and for micronuclei in mouse bone marrow.

Both candesartan and its O-deethyl metabolite tested positive for genotoxicity in the in vitro CHL chromosomal aberration assay. Neither compound tested positive in the Ames microbial mutagenesis assay or in the in vitro mouse lymphoma cell assay. Candesartan (but not its O-deethyl metabolite) was also evaluated in vivo in the mouse micronucleus test and in vitro in the Chinese hamster ovary (CHO) gene mutation assay, in both cases with negative results. Candesartan cilexetil was evaluated in the Ames test, the in vitro mouse lymphoma cell assay, the in vivo rat hepatocyte unscheduled DNA synthesis assay and the in vivo mouse micronucleus test, in each case with negative results. Candesartan cilexetil was not evaluated in the CHL chromosomal aberration or CHO gene mutation assays.

When hydrochlorothiazide was tested alone, positive results were obtained in vitro in the CHO sister chromatid exchange (clastogenicity) and mouse lymphoma cell (mutagenicity) assays and in the Aspergillus nidulans non-disjunciton assay. Hydrochorothiazide was not genotoxic in vitro in the Ames test for point mutations and the CHO test for chromosomal aberrations, or in vivo in assays using mouse germinal cell chromosomes, Chinese hamster bone marrow chromosomes, and the Drosophila sex-linked recessive lethal trait gene.

No fertility studies have been conducted with the combination of candesartan cilexetil and hydrochlorothiazide. Fertility and reproductive performance were not affected in studies with male and female rats given oral doses of up to 300 mg candesartan cilexetil/kg/day (83 times the maximum daily human dose of 32 mg on a body surface area basis). Hydrochlorothiazide had no adverse effects on the fertility of mice and rats of either sex in studies wherein these species were exposed, via their diet, to doses of up to 100 and 4 mg/kg, respectively, prior to conception and throughout gestation.

Pregnancy

Pregnancy Categories C (first trimester) and D (second and third trimesters). See WARNINGS, Fetal/Neonatal Morbidity and Mortality.

Nursing Mothers

It is not known whether candesartan is excreted in human milk, but candesartan has been shown to be present in rat milk. Thiazides appear in human milk. Because of the potential for adverse effects on the nursing infant, a decision should be made whether to discontinue nursing or discontinue the drug, taking into account the importance of the drug to the mother.

Pediatric Use

Safety and effectiveness in pediatric patients have not been established.

Geriatric Use

Of the total number of subjects in all clinical studies of ATACAND HCT (2831), 611 (22%) were 65 and over, while 94 (3%) were 75 and over. No overall differences in safety or effectiveness were observed between these subjects and younger subjects. Other reported clinical experience has not identified differences in responses between the elderly and younger patients, but greater sensitivity of some older individuals cannot be ruled out.

Hydrochlorothiazide is known to be substantially excreted by the kidney, and the risk of toxic reactions to this drug may be greater in patients with impaired renal function.

ADVERSE REACTIONS

Candesartan Cilexetil-Hydrochlorothiazide

ATACAND HCT has been evaluated for safety in more than 2800 patients treated for hypertension. More than 750 of these patients were studied for at least six months and more than 500 patients were treated for at least one year. Adverse experiences have generally been mild and transient in nature and have only infrequently required discontinuation of therapy. The overall incidence of adverse events reported with ATACAND HCT was comparable to placebo. The overall frequency of adverse experiences was not related to dose, age, gender, or race.

In placebo-controlled trials that included 1089 patients treated with various combinations of candesartan cilexetil (doses of 2-32 mg) and hydrochlorothiazide (doses of 6.25-25 mg) and 592 patients treated with placebo, adverse events, whether or not attributed to treatment, occurring in greater than 2% of patients treated with ATACAND HCT and that were more frequent for ATACAND HCT than placebo were: Respiratory System Disorder: upper respiratory tract infection (3.6% vs 3.0%); Body as a Whole: back pain (3.3% vs 2.4%); influenza-like symptoms (2.5% vs 1.9%); Central/Peripheral Nervous System: dizziness (2.9% vs 1.2%).

The frequency of headache was greater than 2% (2.9%) in patients treated with ATACAND HCT but was less frequent than the rate in patients treated with placebo (5.2%).

Other adverse events that have been reported, whether or not attributed to treatment, with an incidence of 0.5% or greater from the more than 2800 patients worldwide treated with ATACAND HCT included: Body as a Whole: inflicted injury, fatigue, pain, chest pain, peripheral edema, asthenia; Central and Peripheral Nervous System: vertigo, paresthesia, hypesthesia; Respiratory System Disorders: bronchitis, sinusitis, pharyngitis, coughing, rhinitis, dyspnea; Musculoskeletal System Disorders: arthralgia, myalgia, arthrosis, arthritis, leg cramps, sciatica; Gastrointestinal System Disorders: nausea, abdominal pain, diarrhea, dyspepsia, gastritis, gastroenteritis, vomiting; Metabolic and Nutritional Disorders: hyperuricemia, hyperglycemia, hypokalemia, increased BUN, creatine phosphokinase increased; Urinary System Disorders: urinary tract infection, hematuria, cystitis; Liver/Biliary System Disorders: hepatic function abnormal, increased transaminase levels; Heart Rate and Rhythm Disorders: tachycardia, palpitation, extrasystoles, bradycardia; Psychiatric Disorders: depression, insomnia, anxiety; Cardiovascular Disorders: ECG abnormal; Skin and Appendages Disorders: eczema, sweating increased, pruritus, dermatitis, rash; Platelet/Bleeding-Clotting Disorders: epistaxis; Resistance Mechanism Disorders: infection, viral infection; Vision Disorders: conjunctivitis; Hearing and Vestibular Disorders: tinnitus.

Reported events seen less frequently than 0.5% included angina pectoris, myocardial infarction and angioedema.

Candesartan Cilexetil

Other adverse experiences that have been reported with candesartan cilexetil, without regard to causality, were: Body as a Whole: fever; Metabolic and Nutritional Disorders: hypertriglyceridemia; Psychiatric Disorders: somnolence; Urinary System Disorders: albuminuria.

Post-Marketing Experience

The following have been very rarely reported in post-marketing experience with candesartan cilexetil:

Digestive: Abnormal hepatic function and hepatitis.

Hematologic: Neutropenia, leukopenia, and agranulocytosis.

Metabolic and Nutritional Disorders: hyperkalemia, hyponatremia.

Renal: renal impairment, renal failure.

Skin and Appendages Disorders: Pruritus and urticaria.

Rare reports of rhabdomyolysis have been reported in patients receiving angiotensin II receptor blockers.

Hydrochlorothiazide

Other adverse experiences that have been reported with hydrochlorothiazide, without regard to causality, are listed below:

Body As A Whole: weakness; Cardiovascular: hypotension including orthostatic hypotension (may be aggravated by alcohol, barbiturates, narcotics or antihypertensive drugs); Digestive: pancreatitis, jaundice (intrahepatic cholestatic jaundice), sialadenitis, cramping, constipation, gastric irritation, anorexia; Hematologic: aplastic anemia, agranulocytosis, leukopenia, hemolytic anemia, thrombocytopenia; Hypersensitivity: anaphylactic reactions, necrotizing angiitis (vasculitis and cutaneous vasculitis), respiratory distress including pneumonitis and pulmonary edema, photosensitivity, urticaria, purpura; Metabolic: electrolyte imbalance, glycosuria; Musculoskeletal: muscle spasm; Nervous System/Psychiatric: restlessness; Renal: renal failure, renal dysfunction, interstitial nephritis; Skin: erythema multiforme including Stevens-Johnson syndrome, exfoliative dermatitis including toxic epidermal necrolysis, alopecia; Special Senses: transient blurred vision, xanthopsia; Urogenital: impotence.

Laboratory Test Findings

In controlled clinical trials, clinically important changes in standard laboratory parameters were rarely associated with the administration of ATACAND HCT.

Creatinine, Blood Urea Nitrogen— Minor increases in blood urea nitrogen (BUN) and serum creatinine were observed infrequently. One patient was discontinued from ATACAND HCT due to increased BUN. No patient was discontinued due to an increase in serum creatinine.

Hemoglobin and Hematocrit—Small decreases in hemoglobin and hematocrit (mean decreases of approximately 0.2 g/dL and 0.4 volume percent, respectively) were observed in patients treated with ATACAND HCT, but were rarely of clinical importance.

Potassium— A small decrease (mean decrease of 0.1 mEq/L) was observed in patients treated with ATACAND HCT. In placebo-controlled trials, hypokalemia was reported in 0.4% of patients treated with ATACAND HCT as compared to 1.0% of patients treated with hydrochlorothiazide or 0.2% of patients treated with placebo.

Liver Function Tests—Occasional elevations of liver enzymes and/or serum bilirubin have occurred.

OVERDOSAGE

Candesartan Cilexetil−Hydrochlorothiazide

No lethality was observed in acute toxicity studies in mice, rats and dogs given single oral doses of up to 2000 mg/kg of candesartan cilexetil or in rats given single oral doses of up to 2000 mg/kg of candesartan cilexetil in combination with 1000 mg/kg of hydrochlorothiazide. In mice given single oral doses of the primary metabolite, candesartan, the minimum lethal dose was greater than 1000 mg/kg but less than 2000 mg/kg.

Limited data are available in regard to overdosage with candesartan cilexetil in humans. The most likely manifestations of overdosage with candesartan cilexetil would be hypotension, dizziness, and tachycardia; bradycardia could occur from parasympathetic (vagal) stimulation. If symptomatic hypotension should occur, supportive treatment should be initiated. For hydrochlorothiazide, the most common signs and symptoms observed are those caused by electrolyte depletion (hypokalemia, hypochloremia, hyponatremia) and dehydration resulting from excessive diuresis. If digitalis has also been administered, hypokalemia may accentuate cardiac arrhythmias.

Candesartan cannot be removed by hemodialysis. The degree to which hydrochlorothiazide is removed by hemodialysis has not been established.

Treatment

To obtain up-to-date information about the treatment of overdose, consult your Regional Poison Control Center. Telephone numbers of certified poison control centers are listed in the Physicians’ Desk Reference (PDR). In managing overdose, consider the possibilities of multiple-drug overdoses, drug-drug interactions, and altered pharmacokinetics in your patient.

DOSAGE & ADMINISTRATION

The usual recommended starting dose of candesartan cilexetil is 16 mg once daily when it is used as monotherapy in patients who are not volume depleted. ATACAND can be administered once or twice daily with total daily doses ranging from 8 mg to 32 mg. Patients requiring further reduction in blood pressure should be titrated to 32 mg. Doses larger than 32 mg do not appear to have a greater blood pressure lowering effect.

Hydrochlorothiazide is effective in doses of 12.5 to 50 mg once daily.

To minimize dose-independent side effects, it is usually appropriate to begin combination therapy only after a patient has failed to achieve the desired effect with monotherapy.

The side effects (See WARNINGS) of candesartan cilexetil are generally rare and apparently independent of dose; those of hydrochlorothiazide are a mixture of dose-dependent phenomena (primarily hypokalemia) and dose-independent phenomena (eg, pancreatitis), the former much more common than the latter.

Therapy with any combination of candesartan cilexetil and hydrochlorothiazide will be associated with both sets of dose-independent side effects.

Replacement Therapy: The combination may be substituted for the titrated components.

Dose Titration by Clinical Effect: A patient whose blood pressure is not controlled on 25 mg of hydrochlorothiazide once daily can expect an incremental effect from ATACAND HCT 16-12.5 mg. A patient whose blood pressure is controlled on 25 mg of hydrochlorothiazide but is experiencing decreases in serum potassium can expect the same or incremental blood pressure effects from ATACAND HCT 16-12.5 mg and serum potassium may improve.

A patient whose blood pressure is not controlled on 32 mg of ATACAND can expect incremental blood pressure effects from ATACAND HCT 32-12.5 mg and then 32-25 mg. The maximal antihypertensive effect of any dose of ATACAND HCT can be expected within 4 weeks of initiating that dose.

Patients with Renal Impairment: The usual regimens of therapy with ATACAND HCT may be followed as long as the patient’s creatinine clearance is > 30 mL/min. In patients with more severe renal impairment, loop diuretics are preferred to thiazides, so ATACAND HCT is not recommended.

Patients with Hepatic Impairment: The usual regimens of therapy with ATACAND HCT may be followed in patients with mild hepatic impairment. In patients with moderate hepatic impairment, consideration should be given to initiation of ATACAND at a lower dose, such as 8 mg. If a lower starting dose is selected for candesartan cilexetil, ATACAND HCT is not recommended for initial titration because the appropriate initial starting dose of candesartan cilexetil cannot be given. (See CLINICAL PHARMACOLOGY, Special Populations, Hepatic Insufficiency).

Thiazide diuretics should be used with caution in patients with hepatic impairment; therefore, care should be exercised with dosing of ATACAND HCT.

ATACAND HCT may be administered with other antihypertensive agents.

ATACAND HCT may be administered with or without food.

HOW SUPPLIED

No. 3825 — Tablets ATACAND HCT 16-12.5, are peach, oval, biconvex, non-film-coated tablets, scored on both sides and coded with ACS on one side. They are supplied as follows:

Bottles of 30 | NDC 54868-4729-0

No. 3826 — Tablets ATACAND HCT 32-12.5, are yellow, oval, biconvex, non-film-coated tablets, scored on both sides and coded with ACJ on one side. They are supplied as follows:

Bottles of 30 | NDC 54868-4869-0

Storage:

Store at 25°C (77°F); excursions permitted to 15-30°C (59-86°F) [see USP Controlled Room Temperature]. Keep container tightly closed.

ATACAND HCT is a trademark of the AstraZeneca group of companies

©AstraZeneca 2008

Manufactured under the license from Takeda Pharmaceutical Company, Ltd.

by: AstraZeneca AB, S-151 85 Södertälje, Sweden

for: AstraZeneca LP, Wilmington, DE 19850

Made in Sweden

Rev. 04/11

Relabeling and Repackaging by:
Physicians Total Care, Inc.
Tulsa, Oklahoma 74146